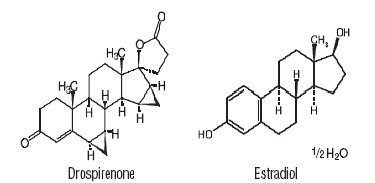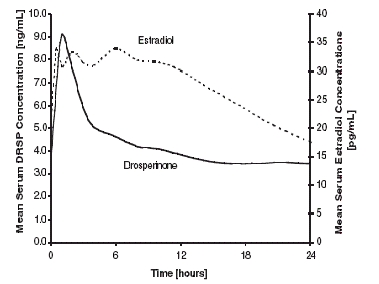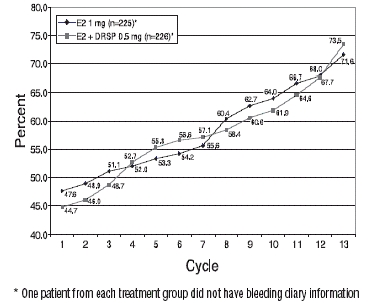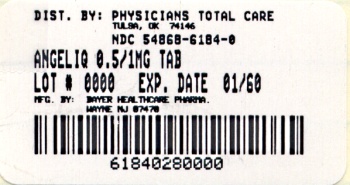 DRUG LABEL: Angeliq
NDC: 54868-6184 | Form: TABLET, FILM COATED
Manufacturer: Physicians Total Care, Inc.
Category: prescription | Type: HUMAN PRESCRIPTION DRUG LABEL
Date: 20090529

ACTIVE INGREDIENTS: ESTRADIOL 1 mg/1 1; DROSPIRENONE 0.5 mg/1 1
INACTIVE INGREDIENTS: STARCH, CORN; FERRIC OXIDE RED; HYPROMELLOSES; LACTOSE MONOHYDRATE; MODIFIED CORN STARCH (1-OCTENYL SUCCINIC ANHYDRIDE); MAGNESIUM STEARATE; POVIDONE K25; TALC; TITANIUM DIOXIDE

ANGELIQ TABLETS
(Drospirenone and Estradiol)
0.5 mg/1 mg

Rx only

PRESCRIBING INFORMATION

Boxed Warnings

Estrogens with or without progestins should not be used for the prevention of cardiovascular disease or dementia. (See WARNINGS, Cardiovascular disorders and Dementia.) The Women's Health Initiative (WHI) study reported increased risks of myocardial infarction, stroke, invasive breast cancer, pulmonary emboli, and deep vein thrombosis in postmenopausal women (50 to 79 years of age) during 5 years of treatment with oral conjugated equine estrogens (CE 0.625mg) combined with medroxyprogesterone acetate (MPA 2.5mg) relative to placebo (see CLINICAL PHARMACOLOGY, Clinical Studies and WARNINGS, Cardiovascular disorders and Malignant neoplasms, Breast cancer.) The Women's Health Initiative Memory Study (WHIMS), a substudy of WHI, reported increased risk of developing probable dementia in postmenopausal women 65 years of age or older during 5.2 years of treatment with conjugated estrogens alone and during 4 years of treatment with oral conjugated estrogens plus medroxyprogesterone acetate, relative to placebo. It is unknown whether this finding applies to younger postmenopausal women. (See CLINICAL PHARMACOLOGY, Clinical Studies, WARNINGS, Dementia and PRECAUTIONS, Geriatric Use.) Other doses of oral conjugated estrogens with medroxyprogesterone acetate, and other combinations and dosage forms of estrogens and progestins were not studied in the WHI clinical trials, and, in the absence of comparable data, these risks should be assumed to be similar. Because of these risks, estrogens with or without progestins should be prescribed at the lowest effective doses and for the shortest duration consistent with treatment goals and risks for the individual woman.

Description

ANGELIQ TABLETS provide a hormone regimen consisting of film coated tablets each containing 0.5 mg of drospirenone and 1 mg of estradiol. The inactive ingredients are lactose monohydrate NF, corn starch NF, modified starch NF, povidone 25000 USP, magnesium stearate NF, hydroxylpropylmethyl cellulose USP, macrogol 6000 NF, talc USP, titanium dioxide USP, and ferric oxide pigment NF.

Drospirenone, (6R,7R,8R,9S,10R,13S,14S,15S,16S,17S)-1,3´,4´,6, 6a,7,8,9,10,11,12,13,14,15,15a,16-hexadecahydro-10,13-dimethylspiro-[ 17H-dicyclopropa[6,7:15,16]cyclopenta[a]phenanthrene- 17,2´(5H)-furan]-3,5´(2H)-dione (CAS) is a synthetic progestational compound and has a molecular weight of 366.5 and a molecular formula of C24H30O3.

Estradiol USP, (Estra-1,3,5(10)-triene-3,17-diol,17ß), has a molecular weight of 272.39 and the molecular formula is C18H24O2. The structural formulas are as follows:

Clinical Pharmacology

Endogenous estrogens are largely responsible for the development and maintenance of the female reproductive system and secondary sexual characteristics. Although circulating estrogens exist in a dynamic equilibrium of metabolic interconversions, estradiol (E2) is the principal intracellular human estrogen and is substantially more potent than its metabolites, estrone and estriol, at the receptor level.

The primary source of estrogen in normally cycling adult women is the ovarian follicle, which secretes 70 to 500 mcg of estradiol daily, depending on the phase of the menstrual cycle. After menopause, most endogenous estrogen is produced by conversion of androstenedione, secreted by the adrenal cortex, to estrone by peripheral tissues. Thus, estrone and the sulfate-conjugated form, estrone sulfate, are the most abundant circulating estrogens in postmenopausal women.

Estrogens act through binding to nuclear receptors in estrogen-responsive tissues. To date, two estrogen receptors have been identified. These will vary in proportion from tissue to tissue.

Circulating estrogens modulate the pituitary secretion of the gonadotropins, luteinizing hormone (LH), and follicle-stimulating hormone (FSH), through a negative feedback mechanism.

Drospirenone (DRSP) is a synthetic progestin and spironolactone analog with antimineralocorticoid activity. In animals and in vitro, drospirenone has antiandrogenic activity, but no glucocorticoid, antiglucocorticoid, estrogenic, or androgenic activity. Progestins counter estrogenic effects by decreasing the number of nuclear estradiol receptors and suppressing epithelial DNA synthesis in endometrial tissue.

Pharmacokinetics

Absorption

Serum concentrations of DRSP reach peak levels approximately 1 hour after administration of ANGELIQ and mean absolute bioavailability of DRSP ranges from 76–85%. Following oral administration, peak serum estradiol concentrations are typically reached 6–8 hours after dosing with ANGELIQ. The oral relative bioavailability of estradiol and DRSP following administration of ANGELIQ is 107% and 102%, respectively when compared to a combination oral suspension.

The pharmacokinetics of DRSP are dose proportional within the dose range of 0.5–4 mg. Following daily dosing of ANGELIQ, steady state DRSP concentrations were observed after 10 days. Mean accumulation ratios for estradiol and DRSP were 1.9 and 2.4, respectively. Mean concentrations at 2 hours for DRSP ranged between 5.9 and 6.7 ng/mL after treatment with ANGELIQ for 365 days. Mean steady state serum DRSP and E2 concentrations are shown in Figure 1, and a summary of primary pharmacokinetic parameters following the administration of 1mg E2/1mg DRSP for 28 days is presented in Table 1.

Figure 1: Mean steady state serum drospirenone and estradiol concentrations following daily oral administration of 1 mg E2/0.5 mg DRSP^1^1DRSP levels are simulated based on data obtained after oral administration of 1 mg DRSP/1 mg Estradiol

Table 1: Mean Steady State Pharmacokinetic Parameters of Tablets Containing Drospirenone (1 mg) and Estradiol (1 mg)
Drospirenone (Mean** ± SD [SD = standard deviation.])
Dose | No. of; Subjects | Cmax [Cmax = Maximum serum concentration,]; (ng/mL) | tmax [tmax = time of maximum serum concentration,]; (h); Median; (range) | AUC [AUC = area under the curve]; (0–24h); (ng•h/mL) | t1/2 [t1/2 = half-life,]; (h)
1mg E2/1mg; DRSP | 14 | 18.3±5.55 | 1.0 (1.0–2.0) | 208±83 | 42.3±21.3
Estradiol (Mean ± SD)
Dose | No. of; Subjects | Cmax; (pg/mL) | tmax; (h); Median; (range) | AUC; (0–24h); (pg•h/mL) | t1/2; (h)
1mg E2/1mg; DRSP | 14 | 43.8±10.0 | 2.5(0.5–12.0) | 665±178 | NA
Estrone (Mean ± SD)
Dose | No. of; Subjects | Cmax; (pg/mL) | tmax; (h); Median; (range) | AUC; (0–24h); (pg•h/mL) | t1/2; (h)
1mg E2/1mg; DRSP | 14 | 245±50.6 | 4.0 (3.0–6.0) | 3814±1159 | 23±6.2

Effect of Food:

The effect of food on the absorption and bioavailability of DRSP and E2 have not been investigated following the administration of ANGELIQ. However, clinical studies with different formulations containing DRSP or E2 have shown that the bioavailability of both drugs is not affected by concomitant food intake.

Distribution

The mean volume of distribution of DRSP is 4.2 L/kg. DRSP does not bind to sex hormone binding globulin (SHBG) or corticosteroid binding globulin (CBG) but binds about 97% to other serum proteins. The distribution of exogenous estrogens is similar to that of endogenous estrogens. Estrogens are widely distributed in the body and are generally found in higher concentrations in the sex hormone target organs. Estradiol circulates in the blood bound to SHBG (37%) and to albumin (61%), while only approximately 1%–2% is unbound.

Metabolism

Mean clearance of DRSP is 1.2 mL/min/kg. DRSP is extensively metabolized after oral administration. The 2 main metabolites of DRSP found in human plasma were identified to be the acid form of DRSP generated by opening of the lactone ring and the 4,5-dihydrodrospirenone-3-sulfate, both of which are formed without the involvement of the cytochrome P450 system. These metabolites were shown not to be pharmacologically active. In in vitro studies with human liver microsomes, DRSP was metabolized only to a minor extent mainly by Cytochrome P450 3A4 (CYP3A4).

Exogenous estrogens are metabolized in the same manner as endogenous estrogens. Circulating estrogens exist in a dynamic equilibrium of metabolic interconversions. These transformations take place mainly in the liver. Estradiol is converted reversibly to estrone, and both can be converted to estriol, which is the major urinary metabolite. Estrogens also undergo enterohepatic recirculation via sulfate and glucuronide conjugation in the liver, biliary secretion of conjugates into the intestine, and hydrolysis in the gut followed by reabsorption. In postmenopausal women, a significant proportion of the circulating estrogens exist as sulfate conjugates, especially estrone sulfate, which serves as a circulating reservoir for the formation of more active estrogens.

Excretion

DRSP serum levels are characterized by a terminal elimination half-life of approximately 36–42 hours. Excretion of DRSP was nearly complete after 10 days and amounts excreted were slightly higher in feces compared to urine. DRSP was extensively metabolized and only trace amounts of unchanged DRSP were excreted in urine and feces. At least 20 different metabolites were observed in urine and feces. About 38% to 47% of the metabolites in urine were glucuronide and sulfate conjugates. In feces, about 17% to 20% of the metabolites were excreted as glucuronides and sulfates. Estradiol, estrone, and estriol are excreted in the urine along with glucuronide and sulfate conjugates.

Special Populations

Geriatric: No pharmacokinetic studies were conducted in the geriatric population.

Pediatric: No pharmacokinetic study for ANGELIQ has been conducted in a pediatric population.

Gender: ANGELIQ is indicated for use in women only.

Race: No studies were done to determine the effect of race on the pharmacokinetics of ANGELIQ.

Patients with Hepatic Impairment: ANGELIQ is contraindicated in patients with hepatic dysfunction (also see BOLDED Warnings). The mean exposure to DRSP in women with moderate liver impairment is approximately three times the exposure in women with normal liver function.

Patients with Renal Impairment: ANGELIQ is contraindicated in patients with renal insufficiency (also see BOLDED Warnings).

The effect of renal insufficiency on the pharmacokinetics of DRSP (3 mg daily for 14 days) and the effects of DRSP on serum potassium levels were investigated in female subjects (n = 28, age 30–65) with normal renal function (11 patients), and mild (10 patients) and moderate (7 patients) renal impairment. All subjects were on a low potassium diet. During the study 7 subjects continued the use of potassium-sparing drugs for the treatment of the underlying illness. On the 14th day (steady-state) of DRSP treatment, the serum DRSP levels were on average 37% higher in the group with moderate renal impairment (CLcr 30–50 mL/min) compared to those in the group with normal renal function. Serum DRSP levels in the group with mild renal impairment (creatinine clearance CLcr, 50–80 mL/min) were comparable to those in the group with normal renal function (CLcr, >80 mL/min). DRSP treatment was well tolerated by all groups. DRSP treatment did not show any clinically significant effect on serum potassium concentration. Although hyperkalemia was not observed in the study, in 5 of the 7 subjects who continued use of potassium sparing drugs during the study, individual mean serum potassium levels increased by up to 0.33 mEq/L. Therefore, potential exists for hyperkalemia to occur in subjects with renal impairment whose serum potassium is in the upper reference range, and who are concomitantly using potassium sparing drugs.

Drug Interactions

Effects of Drospirenone on Other Drugs

Metabolic Interactions

Metabolism of DRSP and potential effects of DRSP on hepatic cytochrome P450 (CYP) enzymes have been investigated in in vitro and in vivo studies (see Metabolism). In in vitro studies, DRSP did not affect turnover of model substrates of CYP1A2 and CYP2D6, but had an inhibitory influence on the turnover of model substrates of CYP1A1, CYP2C9, CYP2C19 and CYP3A4 with CYP2C19 being the most sensitive enzyme. The potential effect of DRSP on CYP2C19 activity was investigated in a clinical pharmacokinetic study using omeprazole as a marker substrate. In the study with 24 postmenopausal women [including 12 women with homozygous (wild type) CYP2C19 genotype and 12 women with heterozygous CYP2C19 genotype] the daily oral administration of 3mg DRSP for 14 days did not affect the systemic clearance of the CYP2C19 substrate omeprazole (40 mg) and the CYP2C19 product 5-hydroxy-omeprazole. Furthermore, no significant effect of DRSP on the systemic clearance of the CYP3A4 product omeprazole sulfone was found. These results demonstrated that DRSP did not inhibit CYP2C19 and CYP3A4 in vivo.

Two further clinical drug-drug interaction studies using simvastatin and midazolam as marker substrates for CYP3A4, were each performed in 24 healthy, postmenopausal women. The results of these studies demonstrated that pharmacokinetics of the CYP3A4 substrates were not influenced by steady-state DRSP concentrations achieved after administration of 3 mg DRSP/day.

Based on the available results of in vivo and in vitro studies, it can be concluded that, at clinical dose level, DRSP is unlikely to interact significantly with cytochrome P450 enzymes.

In vitro and in vivo studies have shown that estrogens are metabolized partially by cytochrome P450 3A4 (CYP3A4). Therefore, inducers or inhibitors of CYP3A4 may affect estrogen drug metabolism. Inducers of CYP3A4 such as St. John's Wort preparations (Hypericum perforatum), phenobarbital, carbamazepine, and rifampin may reduce plasma concentrations of estrogens, possibly resulting in a decrease in therapeutic effects and/or changes in the uterine bleeding profile. Inhibitors of CYP3A4 such as erythromycin, clarithromycin, ketoconazole, itraconazole, ritonavir and grapefruit juice may increase plasma concentrations of estrogens and may result in side effects.

Co-Administration with Drugs that Have the Potential to Increase Serum Potassium

There is a potential for an increase in serum potassium in women taking drospirenone with other drugs that may affect electrolytes, such as angiotensin converting enzyme (ACE) inhibitors, angiotensin receptor blockers, or non-steroidal anti-inflammatory drugs (NSAIDs).

Electrolytes were studied in 230 postmenopausal women with hypertension and/or diabetes mellitus requiring an ACE inhibitor or angiotensin receptor blocker (ARB). Of these, 26 patients had a creatinine clearance >50 mL/min to <80 mL/min. Patients were given 1 mg estradiol (E2) and 3 mg drospirenone (DRSP) (n=112) or placebo (n=118) over 28 days. Non-diabetic patients also received ibuprofen 1200 mg/day for 5 days during the study. There was a single case of serum potassium >6.0 mEq/L and a single case of serum sodium <130 mEq/L on treatment, both occurring following five days of ibuprofen therapy in two women taking E2/DRSP. Serum potassium levels ≥5.5 mEq/L were observed in 8 (7.3%) E2/DRSP-treated subjects (3 diabetic and 5 non-diabetic) and in 3 (2.6%) placebo-treated subjects (2 diabetic and 1 non-diabetic). After 28 days of exposure, the mean change from baseline in serum potassium was 0.11 mEq/L for the E2/DRSP group and 0.08 mEq/L for the placebo group. None of the subjects with serum potassium levels ≥5.5 mEq/L had cardiovascular adverse events. A drug-drug interaction study of DRSP 3 mg/estradiol (E2) 1 mg versus placebo was performed in 24 mildly hypertensive postmenopausal women taking enalapril maleate 10 mg twice daily. Potassium levels were obtained every other day for a total of 2 weeks in all subjects. Mean serum potassium levels in the DRSP/E2 treatment group relative to baseline were 0.22 mEq/L higher than those in the placebo group. Serum potassium concentrations also were measured at multiple timepoints over 24 hours at baseline and on Day 14. On Day 14, the ratios for serum potassium Cmax and AUC in the DRSP/E2 group to those in the placebo group were 0.955 (90% CI: 0.914, 0.999) and 1.010 (90% CI: 0.944, 1.080), respectively. No patient in either treatment group developed hyperkalemia (serum potassium concentrations >5.5 mEq/L).

Of note, occasional or chronic use of NSAID medication was not restricted in any of the ANGELIQ clinical trials.

Clinical Studies

Support for the indications

Support for treatment of vasomotor symptoms and vaginal and vulvar atrophy was shown through bioequivalence of the E2 component of the combination product with a currently marketed E2 product (Estrace®). The multiple-dose bioequivalence study evaluated the bioequivalence of E2 from a tablet containing DRSP (2 mg) and E2 (1 mg) relative to Estrace (1 mg) tablet. DRSP/E2 tablets met the criteria for bioequivalence to Estrace.

Effects on Endometrium

In a one year clinical trial of 1,142 postmenopausal subjects treated with E2 alone or E2 + 0.5, 1, 2, or 3 mg DRSP, endometrial biopsies were performed on 966 (84.6%) subjects during the treatment period. Eight subjects in the E2 monotherapy group developed endometrial hyperplasia (4 simple hyperplasia with no cytological atypia, 3 complex hyperplasia with no cytological atypia, and 1 complex hyperplasia with cytological atypia), and one subject in the 1 mg E2 + 2 mg DRSP group developed simple hyperplasia with no cytological atypia. Table 2 shows that there were no diagnoses of endometrial hyperplasia in the ANGELIQ group.

Table 2: Incidence of Endometrial Hyperplasia after up to 12 Months of Treatment
 | E2 1 mg | ANGELIQ
Total No. Subjects | 226 | 227
Total No. of; On-Treatment Biopsies | 197 (87.2%) | 191 (84.1%)
Hyperplasia | 8 (4.0%) | 0 (0%)

Effects on Uterine Bleeding or Spotting

In a cumulative analysis performed over 12 months in a double blind trial, the proportions of women with amenorrhea increased and at one year, 73.5% of subjects on ANGELIQ had amenorrhea. Results are shown in Figure 2.

Figure 2: Cumulative proportion of subjects with amenorrhea at a given cycle through cycle 13, LOCF

Women's Health Initiative Studies

The Women's Health Initiative (WHI) enrolled a total of 27,000 predominantly healthy postmenopausal women to assess the risks and benefits of either the use of 0.625 mg conjugated equine estrogens (CE) per day alone or the use of 0.625 mg conjugated equine estrogens plus 2.5 mg medroxyprogesterone acetate (MPA) per day compared to placebo in the prevention of certain chronic diseases. The primary endpoint was the incidence of coronary heart disease (CHD) (nonfatal myocardial infarction and CHD death), with invasive breast cancer as the primary adverse outcome studied. A "global index" included the earliest occurrence of CHD, invasive breast cancer, stroke, pulmonary embolism (PE), endometrial cancer, colorectal cancer, hip fracture, or death due to other cause. The study did not evaluate the effects of CE or CE/MPA on menopausal symptoms.

The CE/MPA sub-study was stopped early because, according to the predefined stopping rule, the increased risk of breast cancer and cardiovascular events exceeded the specified benefits included in the "global index". Results of the CE/MPA sub-study, which included 16,608 women (average age of 63 years, range 50 to 79; 83.9% White, 6.5% Black, 5.5% Hispanic), after an average follow-up of 5.2 years are presented in Table 3 below:

Table 3: Relative and Absolute Risk Seen in the CE/MPA Substudy of WHI
Eventc | Relative Risk CE/MPA vs placebo at 5.2 Years (95% CI) | Placebo; n = 8102 | CE/MPA; n = 8506
Eventc | Relative Risk CE/MPA vs placebo at 5.2 Years (95% CI) | Absolute Risk per; 10,000 Person-years
CHD events; Non-fatal MI; CHD death | 1.29 (1.02–1.63); 1.32 (1.02–1.72); 1.18 (0.70–1.97) | 30; 23; 6 | 37; 30; 7
Invasive breast cancer | 1.26 (1.00–1.59) | 30 | 38
Stroke | 1.41 (1.07–1.85) | 21 | 29
Pulmonary embolism | 2.13 (1.39–3.25) | 8 | 16
Colorectal cancer | 0.63 (0.43–0.92) | 16 | 10
Endometrial cancer | 0.83 (0.47–1.47) | 6 | 5
Hip fracture | 0.66 (0.45–0.98) | 15 | 10
Death due to causes other than the events above | 0.92 (0.74–1.14) | 40 | 37
Global Index | 1.15 (1.03–1.28) | 151 | 170
Deep vein thrombosis [not included in Global Index] | 2.07 (1.49–2.87) | 13 | 26
Vertebral fractures | 0.66 (0.44–0.98) | 15 | 9
Other osteoporotic fractures | 0.77 (0.69–0.86) | 170 | 131

For those outcomes included in the "global index," absolute excess risks per 10,000 person-years in the group treated with CE/MPA were 7 more CHD events, 8 more strokes, 8 more PEs, and 8 more invasive breast cancers, while absolute risk reductions per 10,000 person-years were 6 fewer colorectal cancers and 5 fewer hip fractures.

The absolute excess risk of events included in the "global index" was 19 per 10,000 person-years. There was no difference between the groups in terms of all-cause mortality. (See Boxed Warnings , Warnings, and Precautions.)

Women's Health Initiative Memory Study

The Women's Health Initiative Memory Study (WHIMS), a substudy of WHI, enrolled 4,532 predominantly healthy postmenopausal women 65 years of age and older (47% were age 65 to 69 years, 35% were 70 to 74 years, and 18% were 75 years of age and older) to evaluate the effects of CE/MPA (0.625 mg conjugated estrogens plus 2.5 mg medroxyprogesterone acetate) on the incidence of probable dementia (primary outcome) compared with placebo.

After an average follow-up of 4 years, 40 women in the estrogen/progestin (45 per 10,000 women-years) and 21 in the placebo group (22 per 10,000 women-years) were diagnosed with probable dementia. The relative risk of probable dementia in the hormone therapy group was 2.05 (95% CI, 1.21 to 3.48) compared to placebo. Differences between groups became apparent in the first year of treatment. It is unknown whether these findings apply to younger postmenopausal women. (See Boxed Warnings and Warnings, 3. Dementia.)

Indications and Usage

ANGELIQ is indicated in women who have a uterus for the:

1. Treatment of moderate to severe vasomotor symptoms associated with the menopause.

2. Treatment of moderate to severe symptoms of vulvar and vaginal atrophy associated with the menopause. When prescribing solely for the treatment of symptoms of vulvar and vaginal atrophy, topical vaginal products should be considered.

Contraindications

Progestogens/estrogens should not be used in individuals with any of the following conditions:

1. Undiagnosed abnormal genital bleeding.

2. Known, suspected, or history of cancer of the breast.

3. Known or suspected estrogen-dependent neoplasia.

4. Active deep vein thrombosis, pulmonary embolism or history of these conditions.

5. Active or recent (e.g., within the past year) arterial thromboembolic disease (e.g., stroke, myocardial infarction).

6. Renal insufficiency.

7. Liver dysfunction or disease.

8. Adrenal insufficiency.

9. ANGELIQ should not be used in patients with known hypersensitivity to its ingredients.

10. Known or suspected pregnancy. There is no indication for ANGELIQ in pregnancy. There appears to be little or no increased risk of birth defects in children born to women who have used estrogens and progestins from oral contraceptives inadvertently during early pregnancy. (See Precautions).

Warnings

ANGELIQ contains 0.5 mg of the progestin drospirenone that has antialdosterone activity, including the potential for hyperkalemia in high-risk patients.

ANGELIQ should not be used in patients with conditions that predispose to hyperkalemia (i.e. renal insufficiency, hepatic dysfunction, and adrenal insufficiency).

Use caution when prescribing ANGELIQ to women who regularly take other medications that can increase potassium, such as NSAIDs, potassium-sparing diuretics, potassium supplements, ACE inhibitors, angiotensin-II receptor antagonists, and heparin. Consider checking serum potassium levels during the first treatment cycle in high-risk patients.

See Boxed Warnings .

1. Cardiovascular disorders

Estrogen and estrogen/progestin therapy has been associated with an increased risk of cardiovascular events such as myocardial infarction and stroke, as well as venous thrombosis and pulmonary embolism (venous thromboembolism or VTE). Should any of these occur or be suspected, estrogens should be discontinued immediately.

Risk factors for cardiovascular disease (e.g., hypertension, diabetes mellitus, tobacco use, hypercholesterolemia, and obesity) and/or venous thromboembolism (e.g., personal history or family history of VTE, obesity, and systemic lupus erythematosus) should be managed appropriately

a. Coronary heart disease and stroke

In the Women's Health Initiative study (WHI), an increase in the number of myocardial infarctions and strokes has been observed in women receiving oral CE compared to placebo. (See Clinical Pharmacology, Clinical Studies sections.)

In the CE/MPA substudy of WHI an increased risk of coronary heart disease (CHD) events (defined as non-fatal myocardial infarction and CHD death) was observed in women receiving CE/MPA compared to women receiving placebo (37 vs 30 per 10,000 person years). The increase in risk was observed in year one and persisted.

In the same substudy of WHI, an increased risk of stroke was observed in women receiving CE/MPA compared to women receiving placebo (29 vs 21 per 10,000 person-years). The increase in risk was observed after the first year and persisted.

In postmenopausal women with documented heart disease (n = 2,763, average age 66.7 years) a controlled clinical trial of secondary prevention of cardiovascular disease (Heart and Estrogen/Progestin Replacement Study; HERS) treatment with CE/MPA-0.625mg/2.5mg per day demonstrated no cardiovascular benefit. During an average follow-up of 4.1 years, treatment with CE/MPA did not reduce the overall rate of CHD events in postmenopausal women with established coronary heart disease. There were more CHD events in the CE/MPA-treated group than in the placebo group in year 1, but not during the subsequent years.

Two thousand three hundred and twenty one women from the original HERS trial agreed to participate in an open label extension of HERS, HERS II. Average follow-up in HERS II was an additional 2.7 years, for a total of 6.8 years overall. Rates of CHD events were comparable among women in the CE/MPA group and the placebo group in HERS, HERS II, and overall.

Large doses of estrogen (5 mg conjugated estrogens per day), comparable to those used to treat cancer of the prostate and breast, have been shown in a large prospective clinical trial in men to increase the risks of nonfatal myocardial infarction, pulmonary embolism, and thrombophlebitis.

b. Venous thromboembolism (VTE)

In the Women's Health Initiative study (WHI), an increase in VTE has been observed in women receiving CE compared to placebo. (See Clinical Pharmacology and Clinical Studies sections.)

In the CE/MPA substudy of WHI, a 2-fold greater rate of VTE, including deep venous thrombosis and pulmonary embolism, was observed in women receiving CE/MPA compared to women receiving placebo. The rate of VTE was 34 per 10,000 woman-years in the CE/MPA group compared to 16 per 10,000 woman-years in the placebo group. The increase in VTE risk was observed during the first year and persisted.

If feasible, estrogens should be discontinued at least 4 to 6 weeks before surgery of the type associated with an increased risk of thromboembolism, or during periods of prolonged immobilization.

2. Malignant neoplasms

a. Endometrial cancer

The use of unopposed estrogens in women with intact uteri has been associated with an increased risk of endometrial cancer. The reported endometrial cancer risk among unopposed estrogen users is about 2- to 12-fold greater than in non-users, and appears dependent on duration of treatment and on estrogen dose. Most studies show no significant increased risk associated with use of estrogens for less than one year. The greatest risk appears associated with prolonged use, with increased risks of 15- to 24-fold for five to ten years or more and this risk has been shown to persist for at least 8 to 15 years after estrogen therapy is discontinued.

Clinical surveillance of all women taking estrogen/progestin combinations is important. Adequate diagnostic measures, including endometrial sampling when indicated, should be undertaken to rule out malignancy in all cases of undiagnosed persistent or recurring abnormal vaginal bleeding. There is no evidence that the use of natural estrogens results in a different endometrial risk profile than synthetic estrogens of equivalent estrogen dose. Adding a progestin to estrogen therapy has been shown to reduce the risk of endometrial hyperplasia, which may be a precursor to endometrial cancer.

b. Breast cancer

The use of estrogens and progestins by postmenopausal women has been reported to increase the risk of breast cancer. The most important randomized clinical trial providing information about this issue is the Women's Health Initiative (WHI) substudy of CE/MPA (see Clinical Pharmacology,Clinical Studies). The results from observational studies are generally consistent with those of the WHI clinical trial and report no significant variation in the risk of breast cancer among different estrogens or progestins, doses, or routes of administration.

The CE/MPA substudy of WHI reported an increased risk of breast cancer in women who took CE/MPA for a mean follow-up of 5.6 years. Observational studies have also reported an increased risk for estrogen/progestin combination therapy, and a smaller increased risk for estrogen alone therapy, after several years of use. In the WHI trial and from observational studies, the excess risk increased with duration of use. From observational studies, the risk appeared to return to baseline in about five years after stopping treatment. In addition, observational studies suggest that the risk of breast cancer was greater, and became apparent earlier, with estrogen/progestin combination therapy as compared to estrogen alone therapy.

In the CE/MPA substudy, 26% of the women reported prior use of estrogen alone and/or estrogen/progestin combination hormone therapy. After a mean follow-up of 5.6 years during the clinical trial, the overall relative risk of invasive breast cancer was 1.24 (95% confidence interval 1.01–1.54), and the overall absolute risk was 41 vs. 33 cases per 10,000 women-years, for CE/MPA compared with placebo. Among women who reported prior use of hormone therapy, the relative risk of invasive breast cancer was 1.86, and the absolute risk was 46 vs. 25 cases per 10,000 women-years, for CE/MPA compared with placebo. Among women who reported no prior use of hormone therapy, the relative risk of invasive breast cancer was 1.09, and the absolute risk was 40 vs. 36 cases per 10,000 women-years for CE/MPA compared with placebo. In the same substudy, invasive breast cancers were larger and diagnosed at a more advanced stage in the CE/MPA group compared with the placebo group. Metastatic disease was rare with no apparent difference between the two groups. Other prognostic factors such as histologic subtype, grade and hormone receptor status did not differ between the groups.

The use of estrogen plus progestin has been reported to result in an increase in abnormal mammograms requiring further evaluation. All women should receive yearly breast examinations by a healthcare provider and perform monthly breast self-examinations. In addition, mammography examinations should be scheduled based on patient age, and risk factors, and prior mammogram results.

3. Dementia

In the estrogen alone Women's Health Initiative Memory Study (WHIMS), a substudy of WHI, 2,947 hysterectomized women aged 65 to 79 years were randomized to CE or placebo.

In the estrogen plus progestin WHIMS substudy, 4,532 postmenopausal women aged 65 to 79 years were randomized to CE/MPA or placebo. In the estrogen alone substudy, after an average follow-up of 5.2 years, 28 women in the estrogen alone group and 19 women in the placebo group were diagnosed with probable dementia. The relative risk of probable dementia for estrogen alone versus placebo was 1.49 (95% CI 0.83–2.66). The absolute risk of probable dementia for estrogen alone versus placebo was 37 versus 25 cases per 10,000 women-years. It is unknown whether these findings apply to younger postmenopausal women. (See Clinical Pharmacology, Clinical Studies and Precautions, I. GERIATRIC USE .)

After an average follow-up of 4 years, 40 women being treated with CE/MPA (1.8%, n = 2,229) and 21 women in the placebo group (0.9%, n = 2,303) received diagnoses of probable dementia. The relative risk for CE/MPA versus placebo was 2.05 (95% confidence interval 1.21–3.48), and was similar for women with and without histories of menopausal hormone use before WHIMS. The absolute risk of proba

ble dementia for CE/MPA versus placebo was 45 versus 22 cases per 10,000 women-years, and the absolute excess risk for CE/MPA was 23 cases per 10,000 women-years. It is unknown whether these findings apply to younger postmenopausal women. (See Clinical Pharmacology, Clinical Studies and Precautions, I. GERIATRIC USE .)

4. Gallbladder disease

A 2- to 4-fold increase in the risk of gallbladder disease requiring surgery in postmenopausal women receiving estrogens has been reported.

5. Hypercalcemia

Estrogen administration may lead to severe hypercalcemia in patients with breast cancer and bone metastases. If hypercalcemia occurs, use of the drug should be stopped and appropriate measures taken to reduce the serum calcium level.

6. Visual abnormalities

Retinal vascular thrombosis has been reported in patients receiving estrogens. Discontinue medication pending examination if there is sudden partial or complete loss of vision, or a sudden onset of proptosis, diplopia, or migraine. If examination reveals papilledema or retinal vascular lesions, estrogens should be permanently discontinued.

Precautions

A. GENERAL

1. Addition of a progestin when a woman has not had a hysterectomy

Studies of the addition of a progestin for 10 or more days of a cycle of estrogen administration or daily with estrogen in a continuous regimen, have reported a lowered incidence of endometrial hyperplasia than would be induced by estrogen treatment alone. Endometrial hyperplasia may be a precursor to endometrial cancer.

There are, however, possible risks that may be associated with the use of progestins with estrogens compared to estrogen-alone regimens. These include a possible increased risk of breast cancer.

2. Elevated blood pressure

In a small number of case reports, substantial increases in blood pressure have been attributed to idiosyncratic reactions to estrogens. In a large, randomized, placebo-controlled clinical trial, a generalized effect of estrogen therapy on blood pressure was not seen. Blood pressure should be monitored at regular intervals with estrogen use.

3. Hypertriglyceridemia

In patients with pre-existing hypertriglyceridemia, estrogen therapy may be associated with elevations of plasma triglycerides leading to pancreatitis and other complications.

4. Impaired liver function and past history of cholestatic jaundice

Estrogens may be poorly metabolized in patients with impaired liver function. For patients with a history of cholestatic jaundice associated with past estrogen use or with pregnancy, caution should be exercised and in the case of recurrence, medication should be discontinued.

The clearance of drospirenone was decreased in patients with moderate hepatic impairment.

5. Hypothyroidism

Estrogen administration leads to increased thyroid-binding globulin (TBG) levels. Patients with normal thyroid function can compensate for the increased TBG by making more thyroid hormone, thus maintaining free T4 and T3 serum concentrations in the normal range. Patients dependent on thyroid hormone replacement therapy who are also receiving estrogens may require increased doses of their thyroid replacement therapy. These patients should have their thyroid function monitored in order to maintain their free thyroid hormone levels in an acceptable range.

6. Fluid retention

Because estrogen and estrogen/progestin therapy may cause some degree of fluid retention, patients with conditions that might be influenced by this factor, such as a cardiac or renal dysfunction, warrant careful observation when estrogens are prescribed.

7. Hypocalcemia

Estrogens should be used with caution in individuals with severe hypocalcemia.

8. Hyponatremia

As an aldosterone antagonist, drospirenone may increase the possibility of hyponatremia in high-risk patients.

9. Ovarian cancer

The CE/MPA substudy of WHI reported that estrogen plus progestin increased the risk of ovarian cancer. After an average follow-up of 5.6 years, the relative risk for ovarian cancer for CE/MPA versus placebo was 1.58 (95% confidence interval 0.77–3.24) but was not statistically significant. The absolute risk for CE/MPA versus placebo was 4.2 versus 2.7 cases per 10,000 women-years. In some epidemiologic studies, the use of estrogen alone, in particular for ten or more years, has been associated with an increased risk of ovarian cancer. Other epidemiologic studies have not found these associations.

10. Exacerbation of endometriosis

Endometriosis may be exacerbated with administration of estrogens.

11. Exacerbation of other conditions

Estrogens may cause an exacerbation of asthma, diabetes mellitus, epilepsy, migraine, porphyria, systemic lupus erythematosus, and hepatic hemangiomas, and should be used with caution in women with these conditions.

B. PATIENT INFORMATION

Physicians are advised to discuss the PATIENT INFORMATION leaflet with patients for whom they prescribe ANGELIQ.

C. LABORATORY TESTS

Estrogen administration should be initiated at the lowest dose for the approved indication and then guided by clinical response, rather than by serum hormone levels (e.g., estradiol, FSH).

D. DRUG/LABORATORY TEST INTERACTIONS

1. Accelerated prothrombin time, partial thromboplastin time, and platelet aggregation time; increased platelet count; increased factors II, VII antigen, VIII antigen, VIII coagulant activity, IX, X, XII, VII–X complex, II–VII–X complex, and beta-thromboglobulin; decreased levels of anti-factor Xa and antithrombin III, decreased antithrombin III activity; increased levels of fibrinogen and fibrinogen activity; increased plasminogen antigen and activity.
2. Increased thyroid-binding globulin (TBG) levels leading to increased circulating total thyroid hormone, as measured by protein-bound iodine (PBI), T4 levels (by column or by radioimmunoassay) or T3 levels by radioimmunoassay. T3 resin uptake is decreased, reflecting the elevated TBG. Free T4 and free T3 concentrations are unaltered. Patients on thyroid replacement therapy may require higher doses of thyroid hormone.
3. Other binding proteins may be elevated in serum (i.e., corticosteroid binding globulin (CBG), sex hormone-binding globulin (SHBG)) leading to increased circulating corticosteroids and sex steroids, respectively. Free hormone concentrations may be decreased. Other plasma proteins may be increased (angiotensinogen/renin substrate, alpha-1-antitrypsin, ceruloplasmin).
4. Increased plasma HDL and HDL-2 subfraction concentrations, reduced LDL cholesterol concentration, increased triglyceride levels.
5. Impaired glucose tolerance.
6. Reduced response to metyrapone test.

E. CARCINOGENESIS, MUTAGENESIS, AND IMPAIRMENT OF FERTILITY

Long-term continuous administration of estrogen, with and without progestin, in women with and without a uterus, has shown an increased risk of endometrial cancer, breast cancer, and ovarian cancer. (See Boxed Warnings , Warnings and Precautions.)

Long-term continuous administration of natural and synthetic estrogens in certain animal species increases the frequency of carcinomas of the breast, uterus, cervix, vagina, testis, and liver. (See Boxed Warnings , Contraindications, and Warnings sections.)

In a 24 month oral carcinogenicity study in mice dosed with 10 mg/kg/day drospirenone alone or 1 + 0.01, 3 + 0.03 and 10 + 0.1 mg/kg/day of drospirenone and ethinyl estradiol, 0.24 to 10.3 times the exposure (AUC of drospirenone) of women taking a 1 mg dose, there was an increase in carcinomas of the harderian gland in the group that received the high dose of drospirenone alone. In a similar study in rats given 10 mg/kg/day drospirenone alone or 0.3 + 0.003, 3 + 0.03 and 10 + 0.1 mg/kg/day drospirenone and ethinyl estradiol, 2.3 to 51.2 times the exposure of women taking a 1 mg dose, there was an increased incidence of benign and total (benign and malignant) adrenal gland pheochromocytomas in the group receiving the high dose of drospirenone. Drospirenone was not mutagenic in a number of in vitro (Ames, Chinese Hamster Lung gene mutation and chromosomal damage in human lymphocytes) and in vivo (mouse micronucleus) genotoxicity tests. Drospirenone increased unscheduled DNA synthesis in rat hepatocytes and formed adducts with rodent liver DNA but not with human liver DNA. (See Warnings section.)

F. PREGNANCY

ANGELIQ should not be used during pregnancy. (See Contraindications.)

G. NURSING MOTHERS

Estrogen administration to nursing mothers has been shown to decrease the quantity and quality of the milk. Detectable amounts of estrogens have been identified in the milk of mothers receiving this drug. Caution should be exercised when ANGELIQ is administered to a nursing woman.

After administration of an oral contraceptive containing drospirenone about 0.02% of the drospirenone dose was excreted into the breast milk of postpartum women within 24 hours. This results in a maximal daily dose of about 3 mcg drospirenone in an infant.

H. PEDIATRIC USE

ANGELIQ is not indicated in children.

I. GERIATRIC USE

There have not been sufficient numbers of geriatric patients involved in clinical studies utilizing ANGELIQ to determine whether those over 65 years of age differ from younger subjects in their response to ANGELIQ.

In the Women's Health Initiative Memory Study, including 4,532 women 65 years of age and older, followed for an average of 4 years, 82% (n = 3,729) were 65 to 74 while 18% (n = 803) were 75 and over. Most women (80%) had no prior hormone therapy use. Women treated with conjugated estrogens plus medroxyprogesterone acetate were reported to have a two-fold increase in the risk of developing probable dementia. Alzheimer's disease was the most common classification of probable dementia in both the conjugated estrogens plus medroxyprogesterone acetate group and the placebo group. Ninety percent of the cases of probable dementia occurred in the 54% of women who were older than 70. (See Warnings, 3. Dementia.)

Adverse Reactions

See Boxed Warnings , Warnings, AND Precautions.

Because clinical trials are conducted under widely varying conditions, adverse reaction rates observed in the clinical trials of a drug cannot be directly compared to rates in the clinical trials of another drug and may not reflect the rates observed in practice. The adverse reaction information from clinical trials does, however, provide a basis for identifying the adverse events that appear to be related to drug use and for approximating rates.

The following are adverse events reported with ANGELIQ occurring in >5% of subjects:

Table 4: Adverse Events Regardless of Drug Relationship Reported at a Frequency of >5% in a 1-year Double-blind Clinical Trial
ADVERSE EVENT | E2 1 MG; (N=226); n (%) | ANGELIQ; (N=227); n (%)
BODY AS A WHOLE
Abdominal pain | 29 (12.8) | 25 (11)
Pain in extremity | 15 (6.6) | 19 (8.4)
Back pain | 11 (4.9) | 16 (7)
Flu syndrome | 15 (6.6) | 16 (7)
Accidental injury | 15 (6.6) | 13 (5.7)
Abdomen enlarged | 17 (7.5) | 16 (7)
Surgery | 6 (2.7) | 12 (5.3)
METABOLIC & NUTRITIONAL DISORDERS
Peripheral edema | 12 (5.3) | 4 (1.8)
NERVOUS SYSTEM
Headache | 26 (11.5) | 22 (9.7)
RESPIRATORY SYSTEM
Upper respiratory infection | 40 (17.7) | 43 (18.9)
Sinusitis | 8 (3.5) | 12(5.3)
SKIN AND APPENDAGES
Breast pain | 34 (15.0) | 43 (18.9)
UROGENITAL
Vaginal hemorrhage | 43 (19.0) | 21 (9.3)
Endometrial disorder | 22 (9.7) | 4 (1.8)
Leukorrhea | 14 (6.2) | 3 (1.3)

The following additional adverse reactions have been reported with

estrogen and or estrogen/progestin therapy:

1. Genitourinary system

Changes in vaginal bleeding pattern and abnormal withdrawal bleeding or flow; breakthrough bleeding, spotting, dysmenorrhea, increase in size of uterine leiomyomata, vaginitis, including vaginal candidiasis, change in amount of cervical secretion, changes in cervical ectropion, ovarian cancer, endometrial hyperplasia, endometrial cancer.

2. Breasts

Tenderness, enlargement, pain, nipple discharge, galactorrhea, fibrocystic breast changes, breast cancer.

3. Cardiovascular

Deep and superficial venous thrombosis, pulmonary embolism, thrombophlebitis, myocardial infarction, stroke, increase in blood pressure.

4. Gastrointestinal

Nausea, vomiting, abdominal cramps, bloating, cholestatic jaundice, increased incidence of gall bladder disease, pancreatitis, enlargement of hepatic hemangiomas.

5. Skin

Chloasma or melasma, which may persist when drug is discontinued, erythema multiforme, erythema nodosum, hemorrhagic eruption, loss of scalp hair, hirsutism, pruritus, rash.

6. Eyes

Retinal vascular thrombosis, intolerance to contact lenses.

7. Central nervous system

Headache, migraine, dizziness, mental depression, chorea, nervousness, mood disturbances, irritability, exacerbation of epilepsy, dementia.

8. Miscellaneous

Increase or decrease in weight, reduced carbohydrate tolerance, aggravation of porphyria, edema, arthralgias, leg cramps, changes in libido, anaphylactoid/anaphylactic reactions including urticaria and angioedema, hypocalcemia, exacerbation of asthma, increased triglycerides.

OVERDOSAGE

In cases of ANGELIQ overdose, monitor serum concentrations of potassium and sodium since drospirenone has antimineralocorticoid properties.

Serious ill effects have not been reported following acute ingestion of large doses of progestin/estrogen-containing oral contraceptives by young children. Overdosage may cause nausea and withdrawal bleeding may occur in females.

Dosage and Administration

The dosage of ANGELIQ is one tablet daily. Women who are already using a product containing estrogen should stop taking that product before starting ANGELIQ.

Use of estrogen, alone or in combination with a progestin, should be limited to the lowest effective dose available and for the shortest duration consistent with treatment goals and risks for the individual woman. Patients should be reevaluated periodically as clinically appropriate (e.g., 3-month to 6-month intervals) to determine if treatment is still necessary (see Boxed Warnings and Warnings sections). For women who have a uterus, adequate diagnostic measures, such as endometrial sampling, when indicated, should be undertaken to rule out malignancy in cases of undiagnosed persistent or recurring abnormal vaginal bleeding.

The lowest effective dose of ANGELIQ has not been determined.

How Supplied

ANGELIQ TABLETS (drospirenone and estradiol) 0.5 mg/1 mg are available as round, biconvex pink film-coated tablets embossed with "CK" inside a hexagon, and supplied in the following packaging:

1 blisters of 28 tablets NDC 54868-6184-0

Storage Conditions

Store at 25° C (77° F); excursions permitted to 15–30° C (59–86° F) [See USP Controlled Room Temperature].

REFERENCES FURNISHED UPON REQUEST

PATIENT INFORMATION

September 2005

ANGELIQ® TABLETS

(drospirenone and estradiol)

(an"ju–le–k')

Read this PATIENT INFORMATION before you start taking ANGELIQ and read what you get each time you refill ANGELIQ. There may be new information. This information does not take the place of talking to your health care provider about your medical condition or your treatment.

BOXED WARNING

WHAT IS THE MOST IMPORTANT INFORMATION I SHOULD KNOW ABOUT ANGELIQ (a combination of estrogen and a progestin)?

Do not use estrogens with or without progestins to prevent heart disease, heart attacks, or strokes.

Using estrogens with or without progestins may increase your chances of getting heart attack, strokes, breast cancer, and blood clots. Using estrogens with or without progestins may increase your risk of dementia. You and your healthcare provider should talk regularly about whether you still need treatment with ANGELIQ.

What is ANGELIQ?

ANGELIQ is a medicine that contains two kinds of hormones, estrogen and progestin.

What is ANGELIQ used for?

ANGELIQ is used after menopause to:

•reduce moderate to severe hot flashes. Estrogens are hormones made by a woman's ovaries. The ovaries normally stop making estrogens when a woman is between 45 to 55 years old. This drop in body estrogen levels causes the "change of life" or menopause (the end of monthly menstrual periods). Sometimes, both ovaries are removed during an operation before natural menopause takes place. The sudden drop in estrogen levels causes "surgical menopause."

When the estrogen levels begin dropping, some women develop very uncomfortable symptoms, such as feelings of warmth in the face, neck, and chest, or sudden strong feelings of heat and sweating ("hot flashes" or "hot flushes"). In some women, the symptoms are mild, and they will not need estrogens. In other women, symptoms can be more severe. You and your health care provider should talk regularly about whether you still need treatment with ANGELIQ.

•treat moderate to severe dryness, itching, and burning in or around the vagina. You and your healthcare provider should talk regularly about whether you still need treatment with ANGELIQ to control these problems. If you use ANGELIQ only to treat dryness, itching, and burning in and around your vagina, talk with your healthcare provider about whether a topical vaginal product would be better for you.

Who should not use ANGELIQ?

Do not use ANGELIQ if you have had your uterus removed (hysterectomy).

ANGELIQ contains a progestin to decrease the chances of getting cancer of the uterus. If you do not have a uterus, you do not need a progestin and you should not use ANGELIQ.

Do not start taking ANGELIQ if you:

- have unusual vaginal bleeding.
- currently have or have had certain cancers. Estrogens may increase the chances of getting certain types of cancers, including cancer of the breast or uterus. If you have or had cancer, talk with your health care provider about whether you should take ANGELIQ.
- had a stroke or heart attack in the past year.
- currently have or have had blood clots.
- have kidney disease, liver disease, or disease of your adrenal glands.
- are allergic to ANGELIQ or any of its ingredients. See the end of this leaflet for a list of ingredients in ANGELIQ.
- think you may be pregnant.

Tell your health care provider:

- if you are breastfeeding. The hormone in ANGELIQ can pass into your milk.
- about all of your medical problems. Your health care provider may need to check you more carefully if you have certain conditions, such as asthma (wheezing), epilepsy (seizures), migraine, endometriosis, lupus, hypertension (high blood pressure) or problems with your heart, liver, thyroid, kidneys, or have high calcium levels in your blood.
- about all the medicines you take, including prescription and nonprescription medicines, vitamins, and herbal supplements. Some medicines may affect how ANGELIQ works. ANGELIQ may also affect how your other medicines work.
- if you are going to have surgery or will be on bed rest. You may need to stop taking estrogens.

How should I take ANGELIQ?

1. Take one tablet every day.
2. Estrogens should be used only as long as needed. The lowest effective dose of ANGELIQ has not been determined. You and your healthcare provider should talk regularly (for example, every 3 to 6 months) about whether you still need treatment with ANGELIQ.

What are the possible side effects of ANGELIQ?

ANGELIQ is different from other hormonal medicines for menopausal symptoms because it contains drospirenone, and drospirenone may increase the potassium or lower the sodium in your blood.

You should not take ANGELIQ if you have kidney, liver or adrenal disease because these conditions may also increase the potassium in your blood. Some other medicines also increase potassium. If you regularly take another medicine that increases potassium levels, talk with your healthcare provider about whether ANGELIQ is right for you. In some situations, your healthcare provider may recommend testing your blood for potassium.

Less common but serious side effects include the following and should be discussed with your healthcare provider to assess your personal risks:

- Breast cancer
- Cancer of the uterus
- Stroke
- Heart attack
- Blood clots
- Dementia
- Gallbladder disease
- Ovarian cancer

These are some of the warning signs of serious side effects:

- Breast lumps
- Unusual vaginal bleeding
- Dizziness and faintness
- Changes in speech
- Severe headaches
- Chest pain
- Shortness of breath
- Pains in your legs
- Changes in vision
- Vomiting

Call your health care provider right away if you get any of these warning signs, or any other unusual symptom that concerns you.

Common side effects include:

- Headache
- Breast pain
- Irregular vaginal bleeding or spotting
- Stomach/abdominal cramps, bloating
- Nausea and vomiting
- Hair loss

Other side effects include:

- High blood pressure
- Liver problems
- High blood sugar
- Fluid retention
- Enlargement of benign tumors of the uterus ("fibroids")
- Vaginal yeast infection

These are not all the possible side effects of ANGELIQ. For more information, ask your health care provider or pharmacist.

What can I do to lower my chances of a serious side effect with ANGELIQ?

Talk with your health care provider regularly about whether you should continue taking ANGELIQ.

See your health care provider right away if you get vaginal bleeding while taking ANGELIQ.

Have a breast exam and mammogram (breast X-ray) every year unless your health care provider tells you something else. If members of your family have had breast cancer or if you have ever had breast lumps or an abnormal mammogram, you may need to have breast exams more often.

If you have high blood pressure, high cholesterol (fat in the blood), diabetes, are overweight, or if you use tobacco, you may have higher chances for getting heart disease. Ask your health care provider for ways to lower your chances for getting heart disease.

General information about safe and effective use of ANGELIQ.

Medicines are sometimes prescribed for conditions that are not mentioned in patient information leaflets. Do not use ANGELIQ for conditions for which it was not prescribed. Do not give ANGELIQ to other people, even if they have the same symptoms you have. It may harm them.

Keep ANGELIQ out of the reach of children

This leaflet summarizes the most important information about ANGELIQ. If you would like more information, talk with your healthcare provider or pharmacist. You can ask for information about ANGELIQ that is written for health professionals. You can get more information by calling our toll free number (1-888-237-5394) or visit www.angeliq-us.com

What are the ingredients in ANGELIQ?

The active ingredients in ANGELIQ are drospirenone (a progestin) and estradiol. ANGELIQ also contains lactose monohydrate NF, corn starch NF, modified starch NF, povidone USP, magnesium stearate NF, hydroxylpropylmethyl cellulose USP, macrogol NF, talc USP, titanium dioxide USP, and ferric oxide pigment NF.

Do not store above 86°F (30°C).

Manufactured for:

Bayer HealthCare Pharmaceuticals Inc.
Wayne, NJ 07470

©2008 Bayer HealthCare Pharmaceuticals Inc.
All rights reserved.

6702400 US 80621990

March 2008

Relabeling of "Additional Barcode Label" by:
Physicians Total Care, Inc.
Tulsa, OK 74146

PACKAGE LABEL

Rx Only

Angeliq® Tablets

(Drospirenone and Estradiol)

0.5 mg/1 mg

— 0.5 mg/1 mg

— 28 tablets

— oral